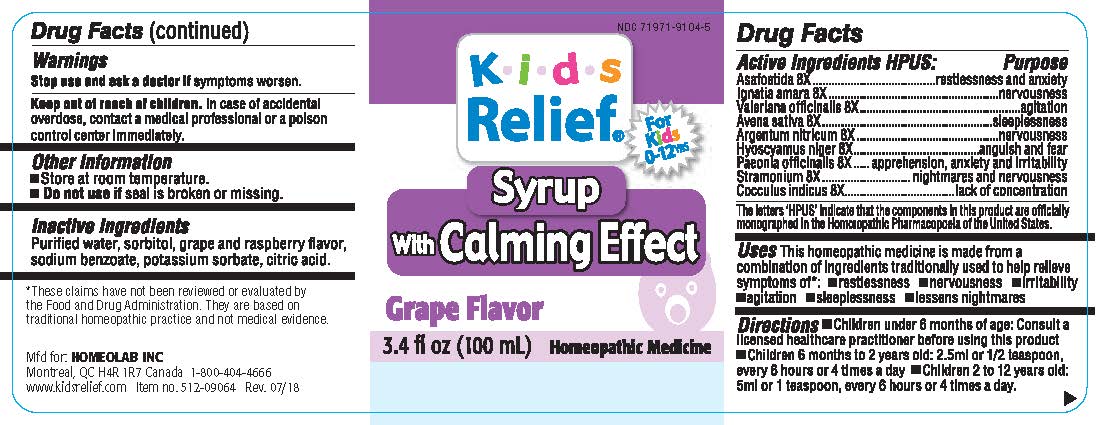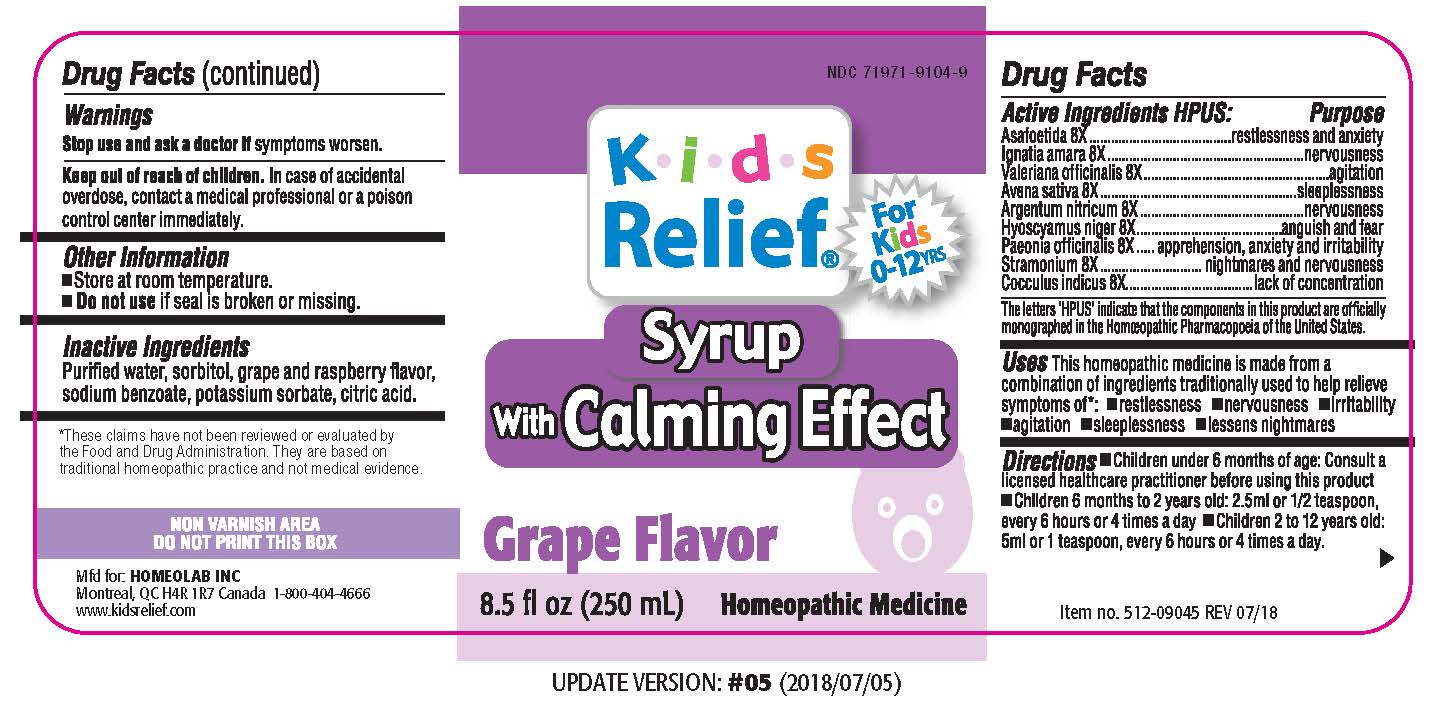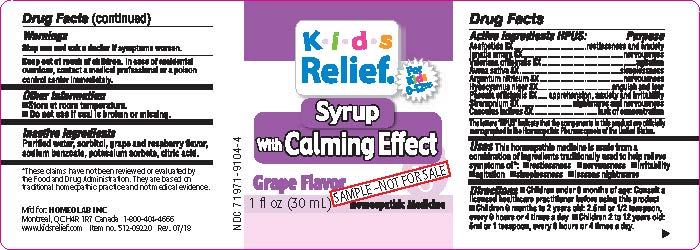 DRUG LABEL: Kids Relief
NDC: 71971-9104 | Form: LIQUID
Manufacturer: Homeolab International (Canada) inc
Category: homeopathic | Type: HUMAN OTC DRUG LABEL
Date: 20191210

ACTIVE INGREDIENTS: ASAFETIDA 8 [hp_X]/100 mL; STRYCHNOS IGNATII SEED 8 [hp_X]/100 mL; VALERIANA OFFICINALIS WHOLE 8 [hp_X]/100 mL; OAT BRAN 8 [hp_X]/100 mL; SILVER NITRATE 8 [hp_X]/100 mL; HYOSCYAMUS NIGER 8 [hp_X]/100 mL; PAEONIA OFFICINALIS ROOT 8 [hp_X]/100 mL; DATURA STRAMONIUM 8 [hp_X]/100 mL; ANAMIRTA COCCULUS WHOLE 8 [hp_X]/100 mL
INACTIVE INGREDIENTS: WATER; SORBITOL; SODIUM BENZOATE; POTASSIUM SORBATE; CITRIC ACID MONOHYDRATE

Active Ingredients HPUS:

Asafoetida 8X

Ignatia amara 8X

Valeriana officinalis 8X

Avena sativa 8X

Argentum nitricum 8X

Hyoscyamus niger 8X

Paeonia officinalis 8X

Stramonium 8X

Cocculus indicus 8X

Purpose of the Drug:

Asafoetida 8X..............................restlessness and anxiety

Ignatia amara 8X.........................nervousness

Valeriana officinalis 8X..................agitation

Avena sativa 8X...........................sleeplessness

Argentum nitricum 8X...................nervousness

Hyoscyamus niger 8X...................anguish and fear

Paeonia officinalis 8X....................apprehension, anxiety and irritability

Stramonium 8X............................nightmares and nervousness

Cocculus indicus 8X......................lack of concentration

The letters 'HPUS' indicate that the components in this product are officially monographed in the

Homeopathic Pharmacopoeia of the United States.

•Uses

This homeopathic medicine is made from a combination of ingredients traditionally used to help relieve symptoms of:

•Restlessness •nervousness •irritability

•agitation •sleeplessness lessens nightmares

Warnings

Stop use and ask a doctor if symptoms worsen.

DOSAGE AND ADMINISTRATION

Directions •Children under 6 months of age: Consult a

licensed healthcare practitioner before using this product

•Children 6 months to 2 years old: 2.5 ml or 1.2 teaspoon,

every 6 hours or 4 times a day •Children 2 to 12 years old:

5ml or 1 teaspoon, every 6 hours or 4 times a day.

Keep out of reach of children. In case of accidental

overdose, contact a medical professional or a poison

control center immediately.

Other information

•Store at room temperature

•Do not use if seal is broken or missing

Inactive ingredients

Purified water, sorbitol, grape and rapsberry flavor,

sodium benzoate, potassium sorbate, citric acid.